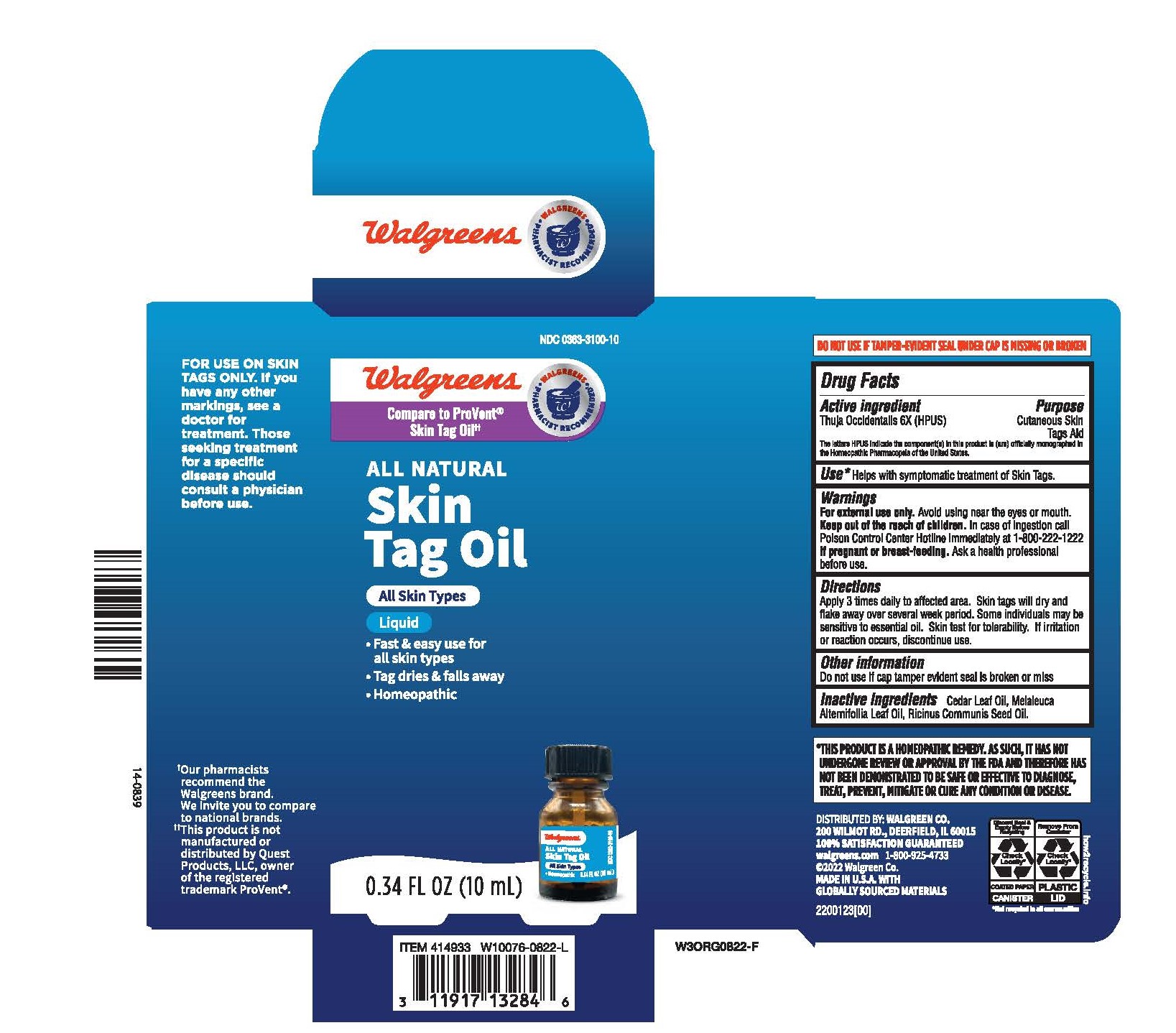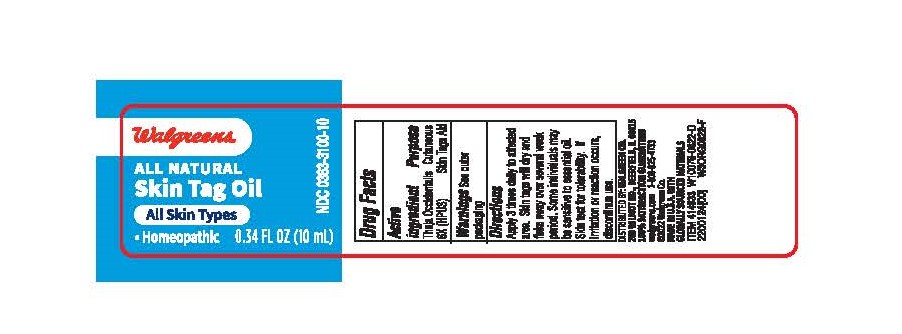 DRUG LABEL: Walgreens Skin Tag Treatment
NDC: 0363-3100 | Form: LIQUID
Manufacturer: Walgreens
Category: homeopathic | Type: HUMAN OTC DRUG LABEL
Date: 20231031

ACTIVE INGREDIENTS: THUJA OCCIDENTALIS LEAFY TWIG 6 [hp_X]/10 mL
INACTIVE INGREDIENTS: TEA TREE OIL; CASTOR OIL; CEDAR LEAF OIL

Walgreens Skin Tag Treatment

ACTIVE INGREDIENT

Thuja Occidentalis 6X (HPUS)

PURPOSE

Cutaneous Skin Tags Aid

INDICATIONS AND USAGE

Helps with symptomatic treatment of Skin Tags

WARNINGS

For External use only. Avoid using near the eyes or mouth

KEEP OUT OF REACH OF CHILDREN

Keep out of the reach of children. In case of ingestion call Poison Control Center Hotline immediately at 1-800-222-1222

PREGNANCY OR BREAST FEEDING

If pregnant or breast- feeding. Ask a health professional before use.

DOSAGE AND ADMINISTRATION

Apply 3 times daily to affected area. Skin tags will dry and flake away over several week period. Some individuals may be sensitive to essential oil. Skin test for tolerability. If irritation or reaction occurs, discontinue use.

Do not use if cap tamper evident seal is broken or miss

INACTIVE INGREDIENT

Cedar Leaf Oil, Melaleuca Alternifollia leaf Oil, Ricinus Communis Seed Oil.